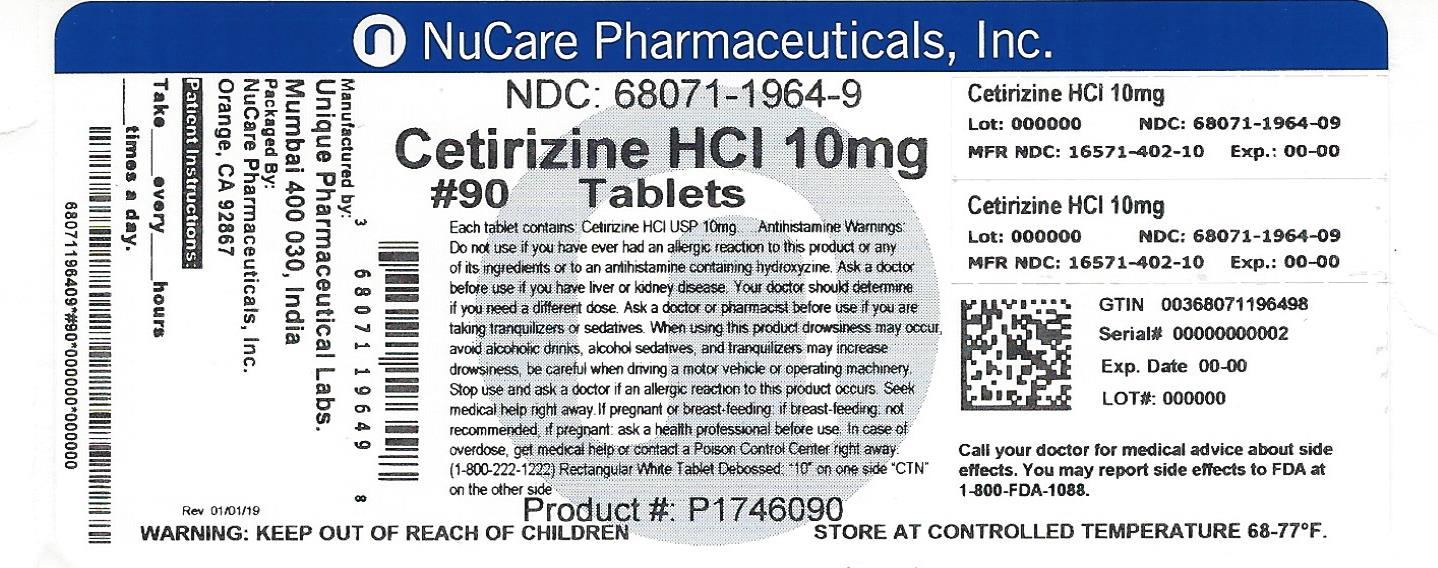 DRUG LABEL: Cetirizine Hydrochloride
NDC: 68071-1964 | Form: TABLET
Manufacturer: NuCare Pharmaceuticals, Inc.
Category: otc | Type: HUMAN OTC DRUG LABEL
Date: 20240715

ACTIVE INGREDIENTS: CETIRIZINE HYDROCHLORIDE 10 mg/1 1
INACTIVE INGREDIENTS: STARCH, CORN; POLYETHYLENE GLYCOL; POVIDONE; TITANIUM DIOXIDE; HYPROMELLOSES; LACTOSE; MAGNESIUM STEARATE

Cetirizine Hydrochloride Tablets, 10 mg, Allergy

Active Ingredients

Active Ingredients (in each tablet) Purpose
Cetirizine HCl 10 mg..............................................................................................Antihistimine

PURPOSE

Uses

Temporarily relieves these symptoms due to hay fever or other upper respiratory allergies

- runny nose
- sneezing
- itchy, watery eyes
- itching of the nose or throat

Warnings

Do Not Use if you have ever had an allergic reaction to this product or any of its ingredients or to an antihistamine containing hydroxyzine.

Ask a doctor before use if you have liver or kidney disease. Your doctor should determine if you need a different dose.

Ask a doctor or pharmacist before use if you are taking tranquilizers or sedatives.

When using this product

- drowsines may occur
- avoid alcoholic drinks
- alcohol, sedatives, and tranquilizers may increase drowsiness
- be careful when driving a motor vehicle or operating machinary.

Stop use and ask a doctor if an allergic reaction to this product occurs. Seek medical help right away.

If pregnant or breast-feeding:

- if breast-feeding: not recommended
- if pregnant: ask a health professional before use.

Keep out of reach of children.

In case of overdose, get medical help or contact Poison Control Center right away.

Directions

Adults and children 6 years and over | one 10 mg tablet once daily, do not take more than one 10 mg tablet in 24 hours. A 5 mg product may be appropriate for less sever symptoms.
Adults 65 years and over | Ask a doctor
Children under 6 years of age | Ask a doctor
Consumers with liver or kidney disease | Ask a doctor

Other Information

store between 20° to 25°C (68° to 77°F)

Inactive Ingredients

Hypromellose, lactose, magnesium stearate, maize starch, polyethylene glycol, povidone, titanium dioxide.

Questions?

Call 1-866-562-4597

Manufactured for PACK Pharmaceuticals, LLC
Buffalo Grove, IL 60089, USA

Manufactured by Unique Pharmaceutical Laboratories (A Div. of J. B. Chemicals & Pharmaceuticals Ltd.),
Mumbai 400 030, India